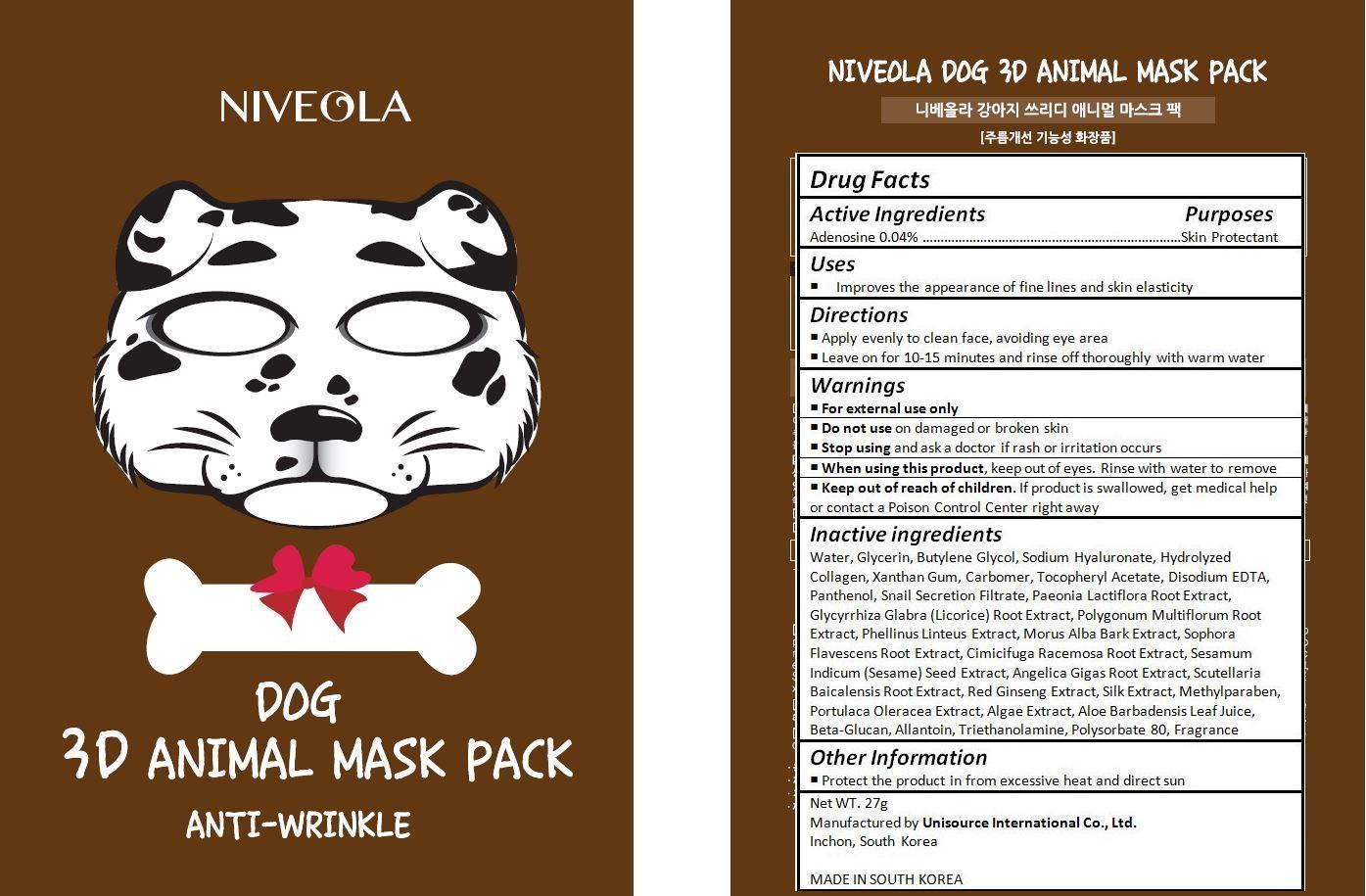 DRUG LABEL: NIVEOLA 3D ANIMAL DOG MASK PACK
NDC: 70133-002 | Form: CREAM
Manufacturer: Unisource International Co., Ltd.
Category: otc | Type: HUMAN OTC DRUG LABEL
Date: 20151008

ACTIVE INGREDIENTS: ADENOSINE 0.01 g/27 g
INACTIVE INGREDIENTS: WATER; GLYCERIN; BUTYLENE GLYCOL; HYALURONATE SODIUM; XANTHAN GUM; CARBOMER HOMOPOLYMER TYPE C (ALLYL PENTAERYTHRITOL CROSSLINKED); .ALPHA.-TOCOPHEROL ACETATE; EDETATE DISODIUM; PANTHENOL; PAEONIA LACTIFLORA ROOT; GLYCYRRHIZA GLABRA; FALLOPIA MULTIFLORA ROOT; PHELLINUS LINTEUS WHOLE; MORUS ALBA BARK; SOPHORA FLAVESCENS ROOT; BLACK COHOSH; SESAME SEED; ANGELICA GIGAS ROOT; SCUTELLARIA BAICALENSIS ROOT; ASIAN GINSENG; BOMBYX MORI FIBER; METHYLPARABEN; PURSLANE; ALOE VERA LEAF; CURDLAN; ALLANTOIN; TROLAMINE; POLYSORBATE 80

Drug Facts

ACTIVE INGREDIENT

Adenosine 0.04%

PURPOSE

Skin Protectant

INDICATIONS AND USAGE

Improves the appearance of fine lines and skin elasticity

DOSAGE AND ADMINISTRATION

Apply evenly to clean face, avoiding eye area
Leave on for 10-15 minutes and rinse off thoroughly with warm water

WARNINGS

For external use only.
Do not use on damaged or broken skin.
When using this product, keep out of eyes. Rinse with water to remove.
Stop using and ask a doctor if rash occurs.

KEEP OUT OF REACH OF CHILDREN

Keep out of reach of the children. If product is swallowed, get medical help or contact a poison control center right away.

INACTIVE INGREDIENT

Water, Glycerin, Butylene Glycol, Sodium Hyaluronate, Hydrolyzed Collagen, Xanthan Gum, Carbomer, Tocopheryl Acetate, Disodium EDTA, Panthenol, Snail Secretion Filtrate, Paeonia Lactiflora Root Extract, Glycyrrhiza Glabra (Licorice) Root Extract, Polygonum Multiflorum Root Extract, Phellinus Linteus Extract, Morus Alba Bark Extract, Sophora Flavescens Root Extract, Cimicifuga Racemosa Root Extract, Sesamum Indicum (Sesame) Seed Extract, Angelica Gigas Root Extract, Scutellaria Baicalensis Root Extract, Red Ginseng Extract, Silk Extract, Methylparaben, Portulaca Oleracea Extract, Algae Extract, Aloe Barbadensis Leaf Juice, Beta-Glucan, Allantoin, Triethanolamine, Polysorbate 80, Fragrance